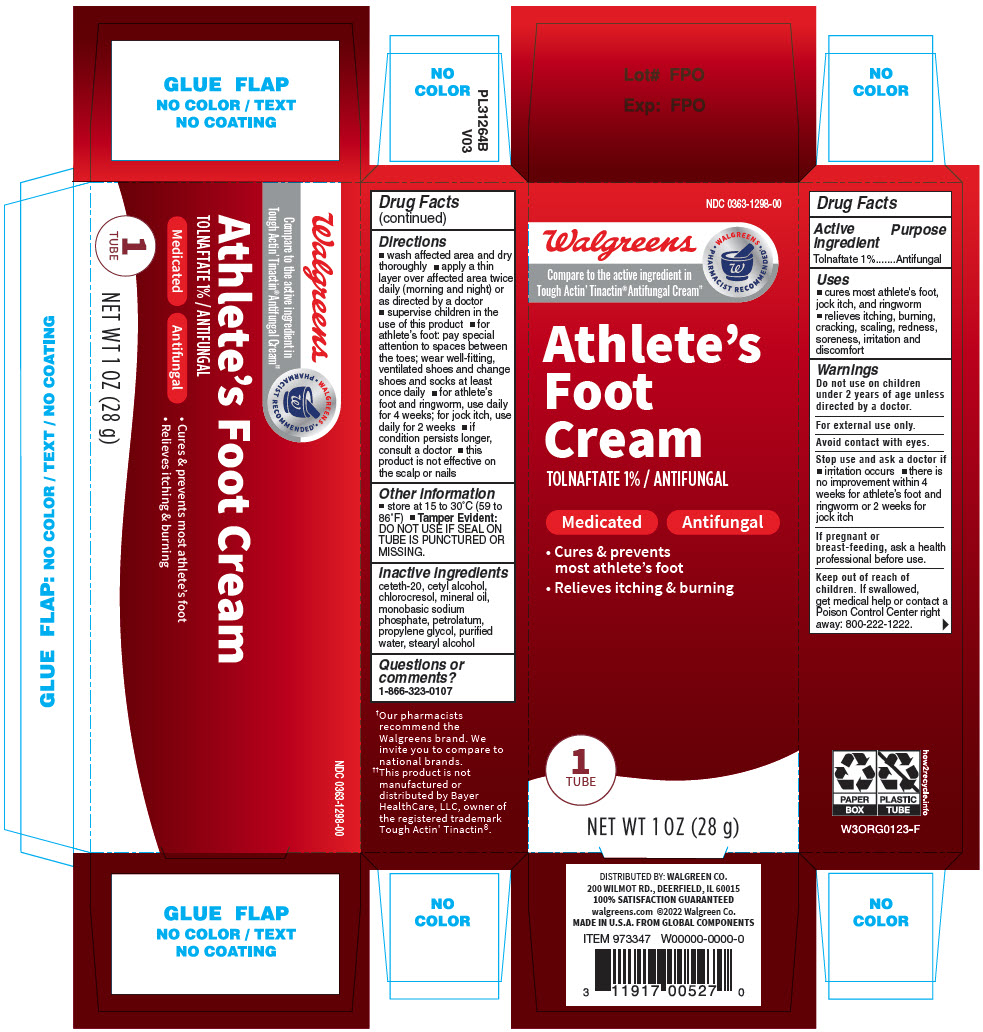 DRUG LABEL: WALGREENS TOLNAFTATE
NDC: 0363-1298 | Form: CREAM
Manufacturer: Walgreen Company
Category: otc | Type: HUMAN OTC DRUG LABEL
Date: 20260128

ACTIVE INGREDIENTS: TOLNAFTATE 10 mg/1 g
INACTIVE INGREDIENTS: MINERAL OIL; CETETH-20; STEARYL ALCOHOL; PROPYLENE GLYCOL; BUTYLATED HYDROXYTOLUENE; CETYL ALCOHOL; SORBITAN MONOSTEARATE; WATER; METHYLPARABEN; PROPYLPARABEN

Walgreens Tolnaftate

Drug Facts

Active ingredient

Tolnaftate 1%

Purpose

Antifungal

Uses

- cures most athlete's foot, jock itch, and ringworm
- relieves itching, burning, cracking, scaling, redness, soreness, irritation and discomfort

Warnings

Do not use on children under 2 years of age unless directed by a doctor.

For external use only.

Avoid contact with eyes.

Stop use and ask a doctor if

- irritation occurs
- there is no improvement within 4 weeks for athlete's foot and ringworm or 2 weeks for jock itch

PREGNANCY OR BREAST FEEDING

If pregnant or breast-feeding, ask a health professional before use.

Keep out of reach of children. If swallowed, get medical help or contact a Poison Control Center right away: 800-222-1222.

Directions

- wash affected area and dry thoroughly
- apply a thin layer over affected area twice daily (morning and night) or as directed by a doctor
- supervise children in the use of this product
- for athlete's foot: pay special attention to spaces between the toes; wear well-fitting, ventilated shoes and change shoes and socks at least once daily
- for athlete's foot and ringworm, use daily for 4 weeks; for jock itch, use daily for 2 weeks
- if condition persists longer, consult a doctor
- this product is not effective on the scalp or nails

Other information

- store at 15 to 30°C (59 to 86°F)
- Tamper Evident: DO NOT USE IF SEAL ON TUBE IS PUNCTURED OR MISSING.

Inactive ingredients

ceteth-20, cetyl alcohol, chlorocresol, mineral oil, monobasic sodium phosphate, petrolatum, propylene glycol, purified water, stearyl alcohol

Questions or comments?

1-866-323-0107

DISTRIBUTED BY:
WALGREEN CO.
200 WILMOT RD.,
DEERFIELD, IL 60015

PRINCIPAL DISPLAY PANEL - 28 g Tube Carton

NDC 0363-1298-00

Walgreens
Compare to the active ingredient in
Tough Actin' Tinactin® Antifungal Cream††

• WALGREENS •
PHARMACIST RECOMMENDED†

Athlete's
Foot
Cream
TOLNAFTATE 1% / ANTIFUNGAL

Medicated
Antifungal

- Cures & prevents
  most athlete's foot
- Relieves itching & burning

1
TUBE

NET WT 1 OZ (28 g)